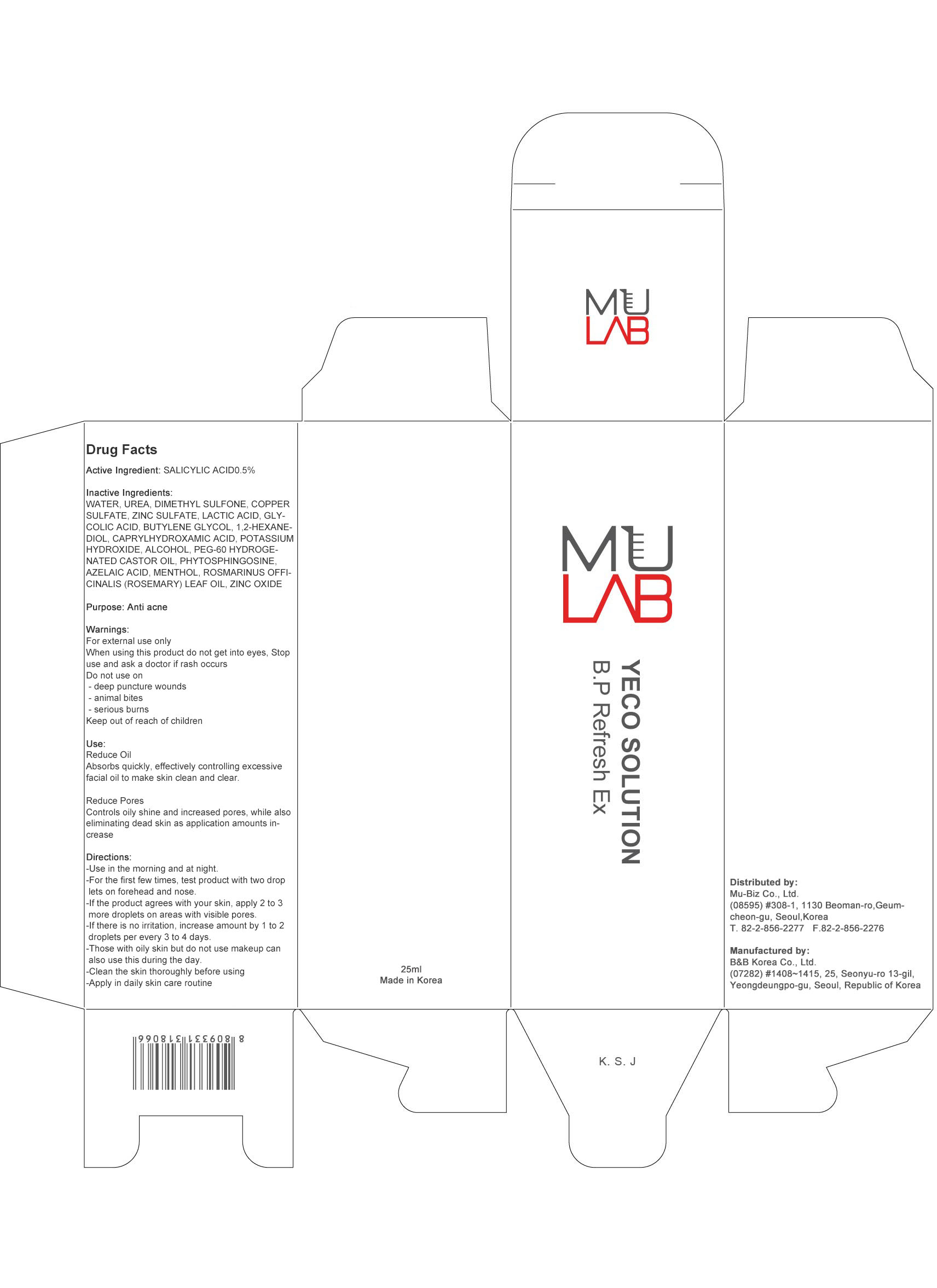 DRUG LABEL: MU LAB YECO SOLU TION BP Refresh EX
NDC: 71164-010 | Form: SOLUTION
Manufacturer: MU-Biz.co,.Ltd
Category: otc | Type: HUMAN OTC DRUG LABEL
Date: 20161230

ACTIVE INGREDIENTS: SALICYLIC ACID 0.10 g/25 mL
INACTIVE INGREDIENTS: WATER; UREA

ACTIVE INGREDIENT

Active Ingredient: SALICYLIC ACID 0.5%

INACTIVE INGREDIENT

Inactive Ingredients: WATER, UREA, DIMETHYL SULFONE, COPPER SULFATE, ZINC SULFATE, LACTIC ACID, GLYCOLIC ACID, BUTYLENE GLYCOL, 1,2-HEXANEDIOL, CAPRYLHYDROXAMIC ACID, POTASSIUM HYDROXIDE, ALCOHOL, PEG-60 HYDROGENATED CASTOR OIL, PHYTOSPHINGOSINE, AZELAIC ACID, MENTHOL, ROSMARINUS OFFICINALIS (ROSEMARY) LEAF OIL, ZINC OXIDE

PURPOSE

Purpose: Anti acne

WARNINGS

Warnings: For external use only. When using this product do not get into eyes, Stop use and ask a doctor if rash occurs. Do not use on - deep puncture wounds - animal bites - serious burns. Keep out of reach of children.

KEEP OUT OF REACH OF CHILDREN

Use

Reduce Oil- Absorbs quickly, effectively controlling excessive facial oil to make skin clean and clear.

Reduce Pores- Controls oily shine and increased pores, while also eliminating dead skin as application amounts increase

Directions

Directions: -Use in the morning and at night. -For the first few times, test product with two droplets on forehead and nose. -If the product agrees with your skin, apply 2 to 3 more droplets on areas with visible pores. -If there is no irritation, increase amount by 1 to 2 droplets per every 3 to 4 days. -Those with oily skin but do not use makeup can also use this during the day. - Clean the skin thoroughly before using - Apply in daily skin care routine